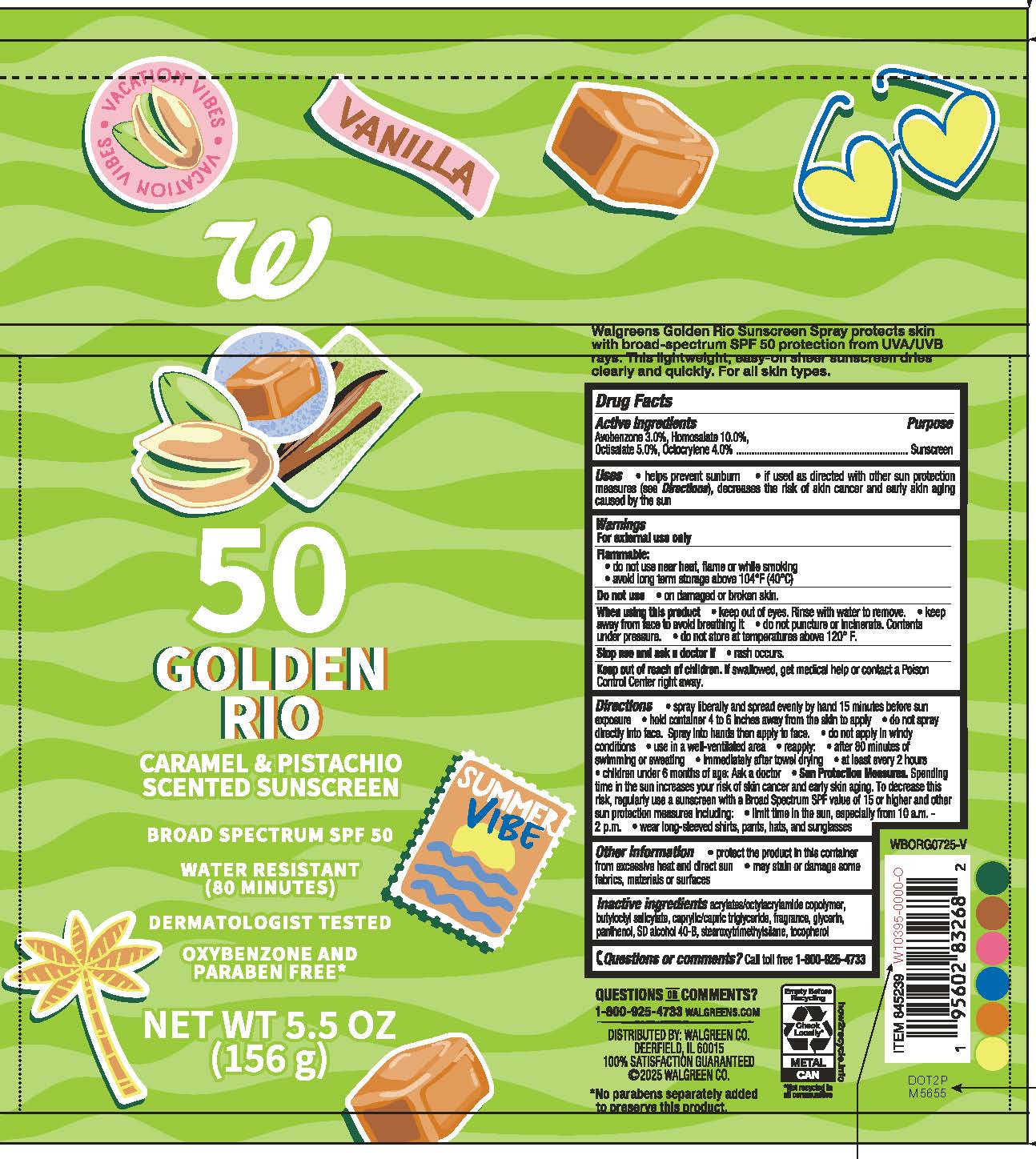 DRUG LABEL: Walgreens 50 Caramel and Pistachio Scented Sunscreen
NDC: 0363-1361 | Form: SPRAY
Manufacturer: WALGREEN COMPANY
Category: otc | Type: HUMAN OTC DRUG LABEL
Date: 20260204

ACTIVE INGREDIENTS: AVOBENZONE 30 mg/1 g; HOMOSALATE 100 mg/1 g; OCTISALATE 50 mg/1 g; OCTOCRYLENE 40 mg/1 g
INACTIVE INGREDIENTS: MEDIUM-CHAIN TRIGLYCERIDES; BUTYLOCTYL SALICYLATE; PANTHENOL; STEAROXYTRIMETHYLSILANE; ALCOHOL; ACRYLATE/ISOBUTYL METHACRYLATE/N-TERT-OCTYLACRYLAMIDE COPOLYMER (75000 MW); .ALPHA.-TOCOPHEROL, DL-; GLYCERIN

Walgreens SPF 50 Caramel and Pistachio Scented Sunscreen

Active Ingredients

Avobenzone 3.0%, Homosalate 10.0%, Octisalate 5.0%, Octocrylene 4.0%

Purpose

Sunscreen

Uses

- helps prevent sunburn
- if used as directed with other sun protetion measures (see Directions), decreases the risk of skin cancer and early skin aging caused by the sun

Warnings

For external use only

FLAMMABLE:

- do not use near heat, flame or while smoking
- avoid long term stoage above 104°F (40°C)

Do not use

• on damaged or broken skin.

When using this product

• keep out of eyes. Rinse with water to remove. • do not puncture or incinerate. Contents under pressure. • do not store at temperatures above 120°F.

Stop use and ask a doctor if

• rash occurs.

Keep out of reach of children.

If swallowed, get medical help or contact a Poison Control Center right away.

Directions

- spray liberally and apply evenly by hand 15 minutes before sun exposure
- hold container 4 to 6 inches away from the skinto apply
- do not spray into face. Spray into hands and then apply to face.
- do not apply in windy conditions
- use in well-ventilated area
- reapply:

• after 80 minutes of swimming or sweating

• immediately after towel drying

• at least every 2 hours

- children under 6 months of age: Ask a doctor
- Sun Protection Measures. Spending time in the sun increases your risk of skin cancer and early skin aging. To decrease this risk, regularly use a sunscreen with a Broad Spectrum SPF value of 15 or higher and other sun protection measures including:

• limit time in the sun, especially from 10 a.m. - 2 p.m.

• wearl long-sleeved shirts, pants, hats, and sunglasses

Other Information

- protect the product in this container from excessive heat and direct sun
- may stain or damage some fabrics, materials or surfaces

Inactive Ingredients

acrylates/octylacrylamide copolymer,
butyloctyl salicylate, caprylic/capric triglyceride, fragrance, glycerin,
panthenol, SD alcohol 40-B, stearoxytrimethylsilane, tocopherol